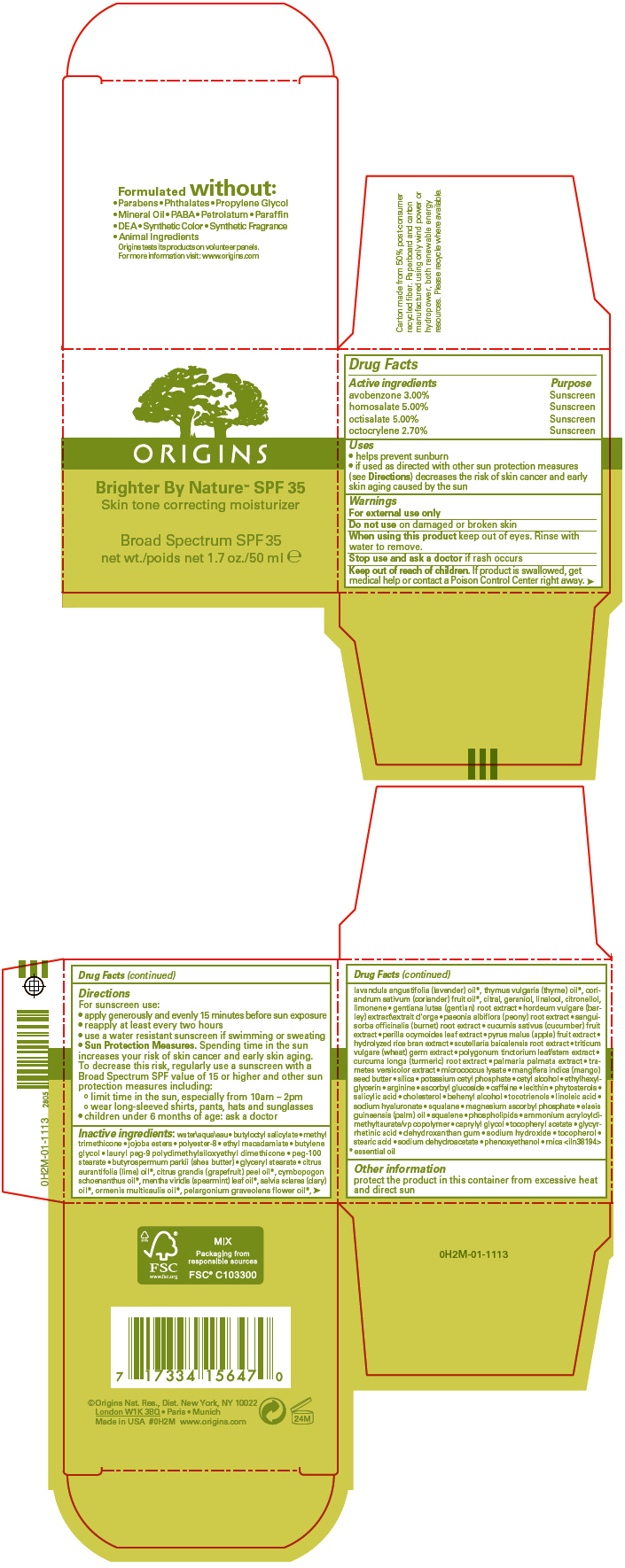 DRUG LABEL: BRIGHTER BY NATURE 
NDC: 59427-008 | Form: CREAM
Manufacturer: ORIGINS NATURAL RESOURCES INC.
Category: otc | Type: HUMAN OTC DRUG LABEL
Date: 20130410

ACTIVE INGREDIENTS: HOMOSALATE 0.0498 g/1 mL; OCTISALATE 0.0498 g/1 mL; AVOBENZONE 0.02988 g/1 mL; OCTOCRYLENE 0.02689 g/1 mL
INACTIVE INGREDIENTS: water; butyloctyl salicylate; methyl trimethicone; ethyl macadamiate; butylene glycol; lauryl peg-9 polydimethylsiloxyethyl dimethicone; peg-100 stearate; shea butter; glyceryl monostearate; lime oil; citrus maxima fruit rind oil; cymbopogon schoenanthus oil; spearmint oil; clary sage oil; pelargonium graveolens flower oil; lavender oil; thyme oil; coriander oil; citral; geraniol; linalool, (+/-)-; .beta.-citronellol, (r)-; gentiana lutea root; paeonia lactiflora root; sanguisorba officinalis root; cucumber; perilla frutescens top; apple; scutellaria baicalensis root; wheat germ; persicaria tinctoria top; turmeric; dulse; mangifera indica seed butter; silicon dioxide; potassium cetyl phosphate; cetyl alcohol; ethylhexylglycerin; arginine; ascorbyl glucoside; caffeine; salicylic acid; cholesterol; docosanol; tocotrienols; linoleic acid; hyaluronate sodium; squalane; magnesium ascorbyl phosphate; palm oil; squalene; ammonium acryloyldimethyltaurate/vp copolymer; caprylyl glycol; .alpha.-tocopherol acetate; enoxolone; sodium hydroxide; tocopherol; stearic acid; sodium dehydroacetate; phenoxyethanol; mica

BRIGHTER BY NATURE™
SPF 35 SKIN TONE CORRECTING MOISTURIZER BROAD SPECTRUM

Drug Facts

ACTIVE INGREDIENT

Active ingredients | Purpose
avobenzone 3.00% | Sunscreen
homosalate 5.00% | Sunscreen
octisalate 5.00% | Sunscreen
octocrylene 2.70% | Sunscreen

Uses

- helps prevent sunburn
- if used as directed with other sun protection measures (see Directions) decreases the risk of skin cancer and early skin aging caused by the sun

Warnings

For external use only

Do not use on damaged or broken skin

When using this product keep out of eyes. Rinse with water to remove.

Stop use and ask a doctor if rash occurs

Keep out of reach of children. If product is swallowed, get medical help or contact a Poison Control Center right away.

Directions

For sunscreen use:

- apply generously and evenly 15 minutes before sun exposure
- reapply at least every two hours
- use a water resistant sunscreen if swimming or sweating
- Sun Protection Measures. Spending time in the sun increases your risk of skin cancer and early skin aging. To decrease this risk, regularly use a sunscreen with a Broad Spectrum SPF value of 15 or higher and other sun protection measures including:
  - limit time in the sun, especially from 10am – 2pm
  - wear long-sleeved shirts, pants, hats and sunglasses
- children under 6 months of age: ask a doctor

Inactive ingredients

water\aqua\eau • butyloctyl salicylate • methyl trimethicone • jojoba esters • polyester-8 • ethyl macadamiate • butylene glycol • lauryl peg-9 polydimethylsiloxyethyl dimethicone • peg-100 stearate • butyrospermum parkii (shea butter) • glyceryl stearate • citrus aurantifolia (lime) oil [essential oil] , citrus grandis (grapefruit) peel oil, cymbopogon schoenanthus oil, mentha viridis (spearmint) leaf oil, salvia sclarea (clary) oil, ormenis multicaulis oil, pelargonium graveolens flower oil, lavandula angustifolia (lavender) oil, thymus vulgaris (thyme) oil, coriandrum sativum (coriander) fruit oil, citral, geraniol, linalool, citronellol, limonene • gentiana lutea (gentian) root extract • hordeum vulgare (barley) extract\extrait d'orge • paeonia albiflora (peony) root extract • sanguisorba officinalis (burnet) root extract • cucumis sativus (cucumber) fruit extract • perilla ocymoides leaf extract • pyrus malus (apple) fruit extract • hydrolyzed rice bran extract • scutellaria baicalensis root extract • triticum vulgare (wheat) germ extract • polygonum tinctorium leaf/stem extract • curcuma longa (turmeric) root extract • palmaria palmata extract • trametes versicolor extract • micrococcus lysate • mangifera indica (mango) seed butter • silica • potassium cetyl phosphate • cetyl alcohol • ethylhexylglycerin • arginine • ascorbyl glucoside • caffeine • lecithin • phytosterols • salicylic acid • cholesterol • behenyl alcohol • tocotrienols • linoleic acid • sodium hyaluronate • squalane • magnesium ascorbyl phosphate • elaeis guineensis (palm) oil • squalene • phospholipids • ammonium acryloyldimethyltaurate/vp copolymer • caprylyl glycol • tocopheryl acetate • glycyrrhetinic acid • dehydroxanthan gum • sodium hydroxide • tocopherol • stearic acid • sodium dehydroacetate • phenoxyethanol • mica <iln38194>

Other information

protect the product in this container from excessive heat and direct sun

PRINCIPAL DISPLAY PANEL - 50 ml Jar Carton

ORIGINS

Brighter By Nature™ SPF 35
Skin tone correcting moisturizer

Broad Spectrum SPF 35
net wt. 1.7 oz./50 ml e